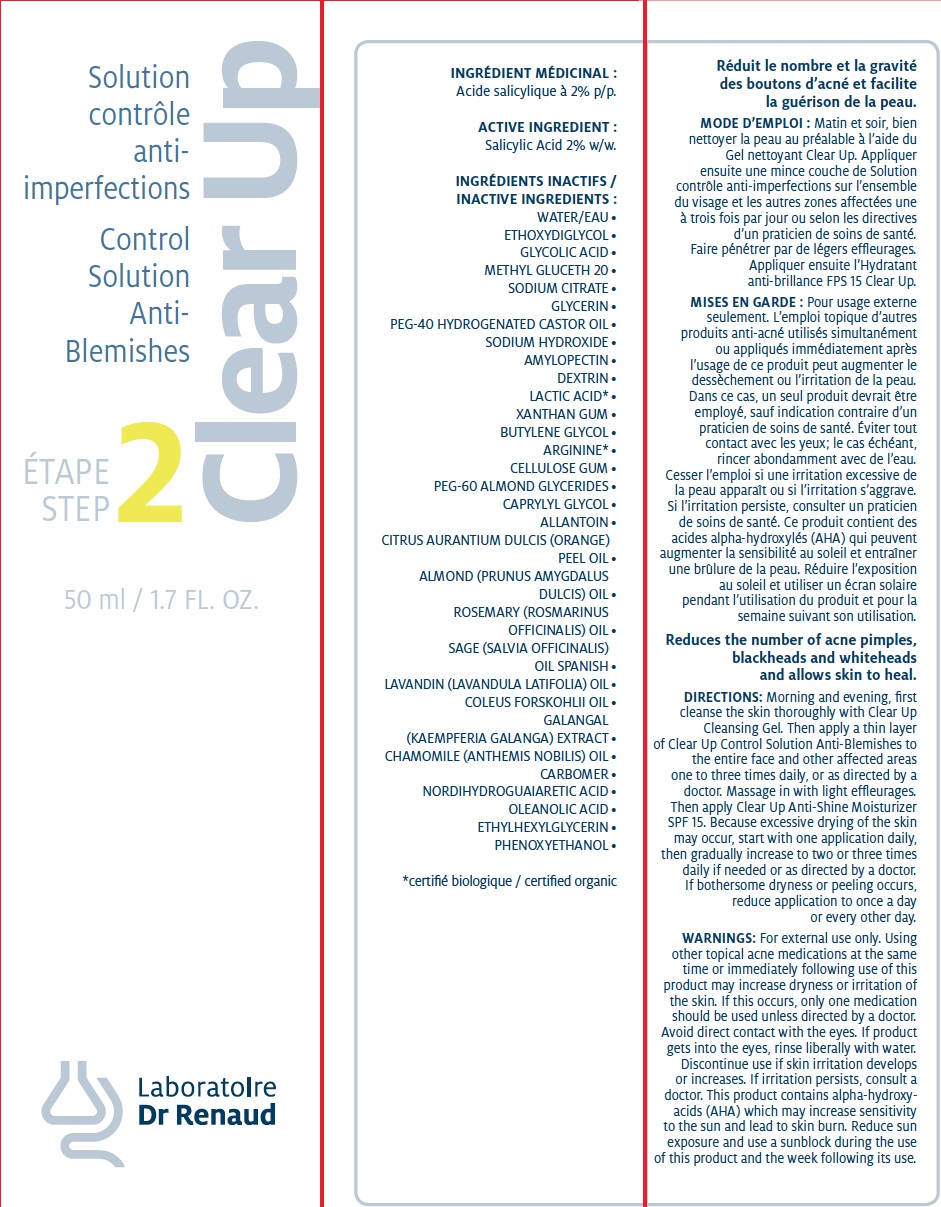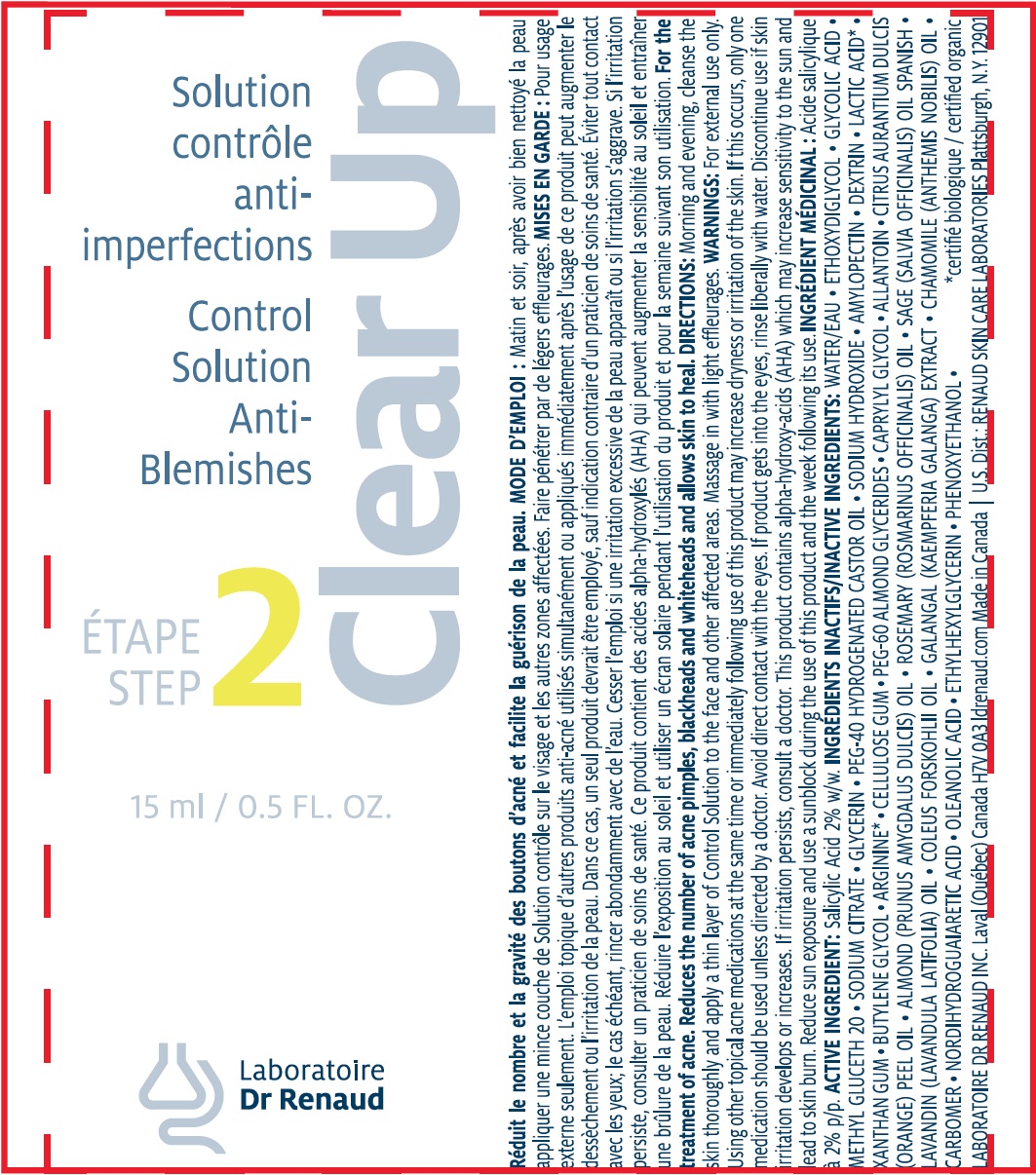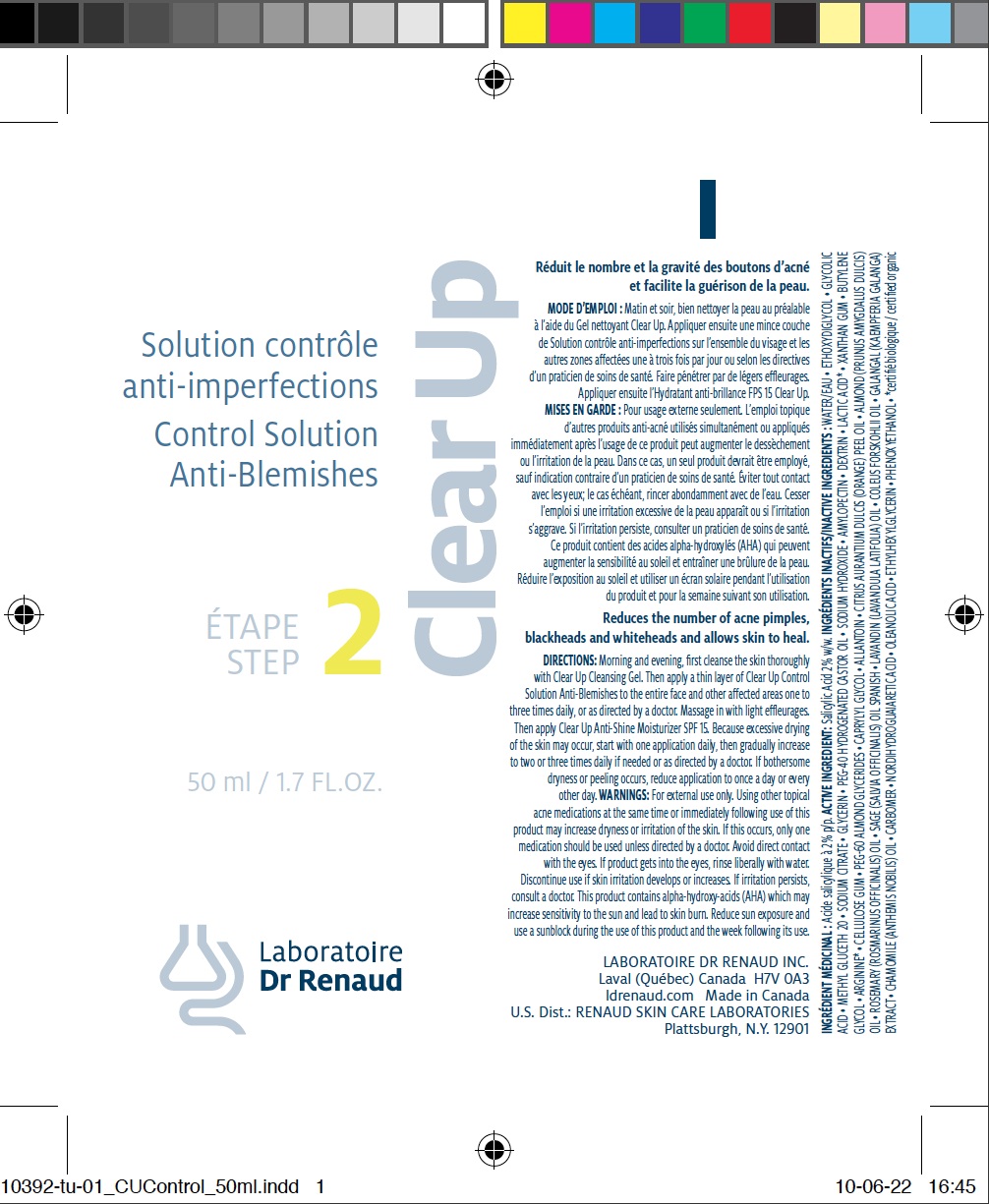 DRUG LABEL: CLEAR UP Control Solution Anti-Blemiches
NDC: 62499-392 | Form: GEL
Manufacturer: Laboratoire Dr. Renaud
Category: otc | Type: HUMAN OTC DRUG LABEL
Date: 20100629

ACTIVE INGREDIENTS: SALICYLIC ACID 2 g/100 g
INACTIVE INGREDIENTS: WATER; DIETHYLENE GLYCOL MONOETHYL ETHER; GLYCOLIC ACID; METHYL GLUCETH-20; SODIUM CITRATE; GLYCERIN; HYDROGENATED CASTOR OIL; SODIUM HYDROXIDE; AMYLOPECTIN; OLEANOLIC ACID; LACTIC ACID; PHENOXYETHANOL; XANTHAN GUM; BUTYLENE GLYCOL; ARGININE; CARBOXYMETHYLCELLULOSE SODIUM; CAPRYLYL GLYCOL; ALLANTOIN; ORANGE OIL; ALMOND OIL; ROSEMARY OIL; SAGE OIL; LAVANDIN OIL; ETHYLHEXYLGLYCERIN; CHAMOMILE FLOWER OIL

Drug Facts

ACTIVE INGREDIENT

Salicylic Acid 2% w/w.

INACTIVE INGREDIENTS

WATER/EAU • ETHOXYDIGLYCOL • GLYCOLIC ACID • METHYL GLUCETH 20 • SODIUM CITRATE • GLYCERIN •
PEG-40 HYDROGENATED CASTOR OIL • SODIUM HYDROXIDE • AMYLOPECTIN • DEXTRIN • LACTIC ACID* • XANTHAN GUM •
BUTYLENE GLYCOL • ARGININE* • CELLULOSE GUM • PEG-60 ALMOND GLYCERIDES • CAPRYLYL GLYCOL • ALLANTOIN •
CITRUS AURANTIUM DULCIS (ORANGE) PEEL OIL • ALMOND (PRUNUS AMYGDALUS DULCIS) OIL • ROSEMARY (ROSMARINUS
OFFICINALIS) OIL • SAGE (SALVIA OFFICINALIS) OIL SPANISH • LAVANDIN (LAVANDULA LATIFOLIA) OIL •
COLEUS FORSKOHLII OIL • GALANGAL (KAEMPFERIA GALANGA) EXTRACT • CHAMOMILE (ANTHEMIS NOBILIS) OIL •
CARBOMER • NORDIHYDROGUAIARETIC ACID • OLEANOLIC ACID • ETHYLHEXYL GLYCERIN • PHENOXYETHANOL

PURPOSE

For the treatment of acne.Reduces the number of acne pimples,blackheads and whiteheads and allows skin to heal.

DIRECTIONS

Morning and evening, first
cleanse the skin thoroughly with CLEAR UP
Cleansing Gel. Then apply a thin layer
of CLEAR UP Control Solution Anti-Blemishes
to the entire face and other affected areas
one to three times daily, or as directed by a
doctor. Massage in with light effleurages.
Then apply CLEAR UP Anti-Shine Moisturizer
SPF 15. Because excessive drying of the skin
may occur, start with one application daily,
then gradually increase to two or three times
daily if needed or as directed by a doctor.
If bothersome dryness or peeling occurs,
reduce application to once a day
or every other day.

WARNINGS

For external use only. Using
other topical acne medications at the same
time or immediately following use of this
product may increase dryness or irritation of
the skin. If this occurs, only one medication
should be used unless directed by a doctor.
Avoid direct contact with the eyes. If product
gets into the eyes, rinse liberally with water.
Discontinue use if skin irritation develops
or increases. If irritation persists, consult a
doctor. This product contains alpha-hydroxyacids
(AHA) which may increase sensitivity
to the sun and lead to skin burn. Reduce sun
exposure and use a sunblock during the use
of this product and the week following its use.

PACKAGE LABEL

image of tube 50ml lable
image of tube 15 ml lable
image of carton 50ml label

INDICATIONS AND USAGE

Enter section text here

Keep out of reach of children.